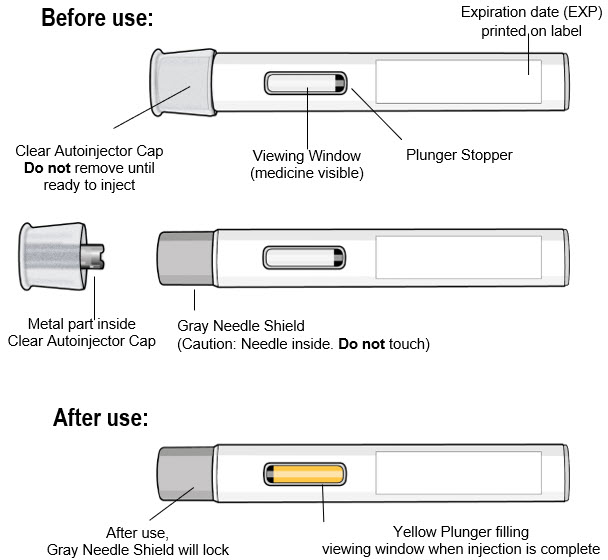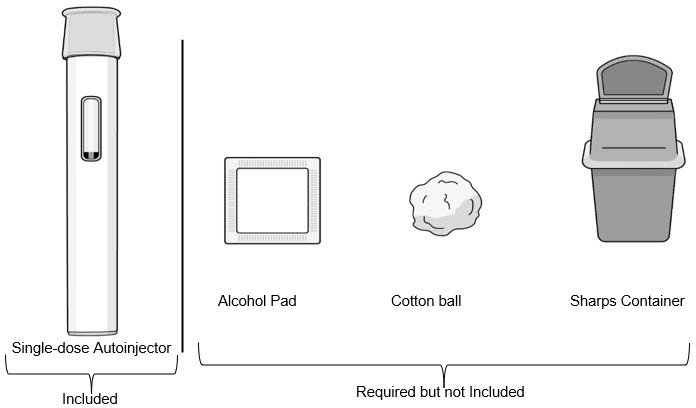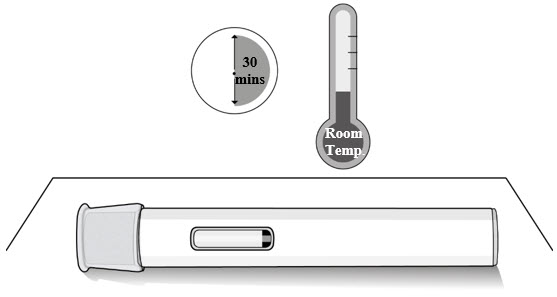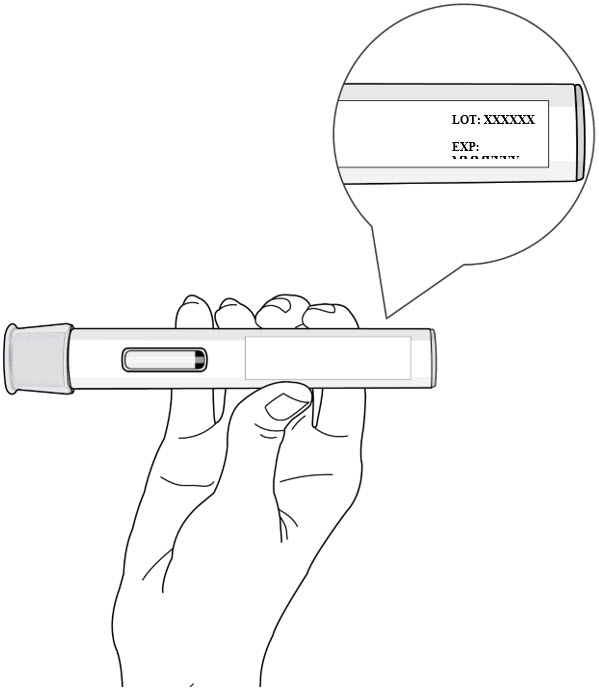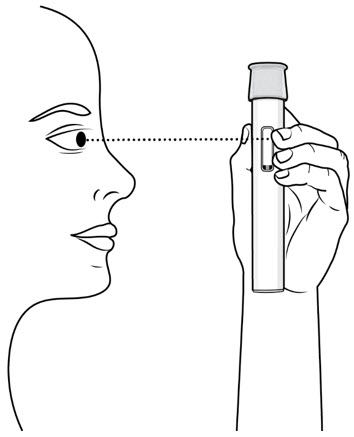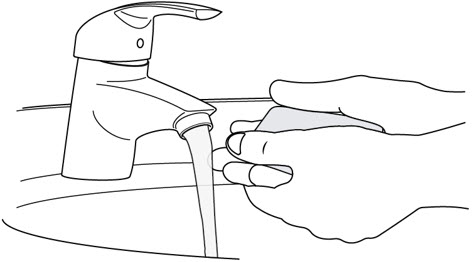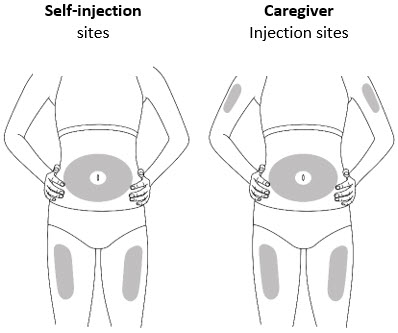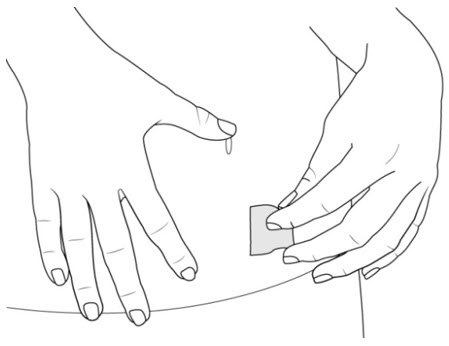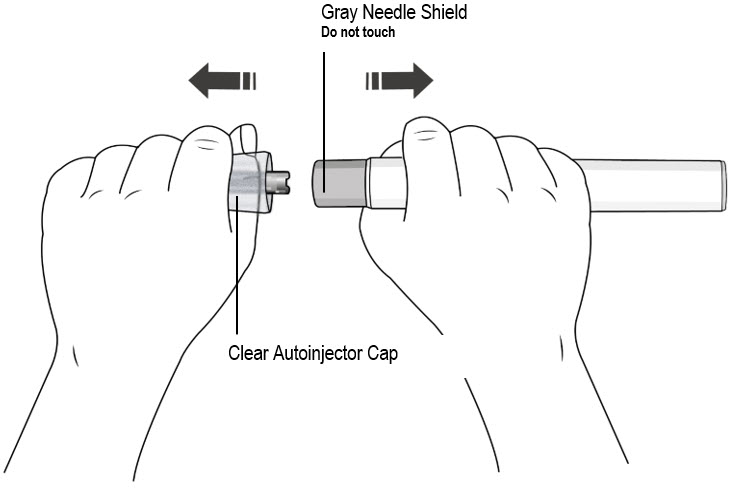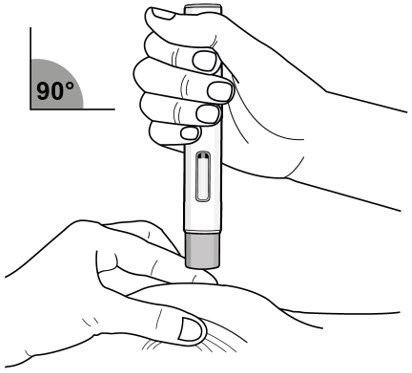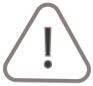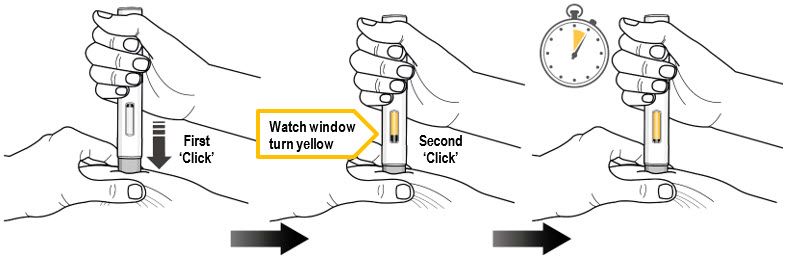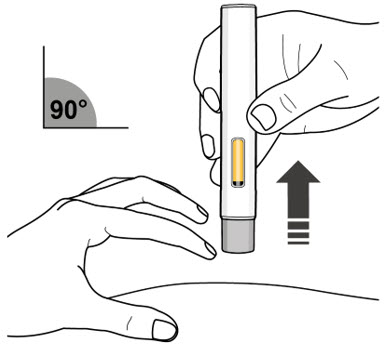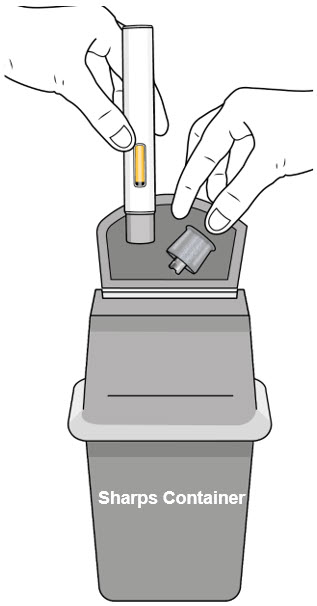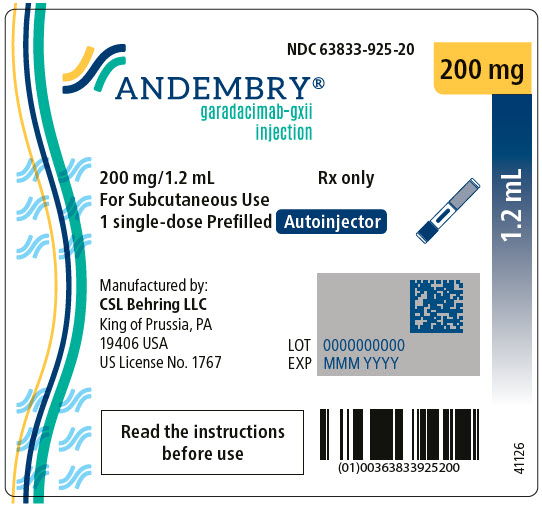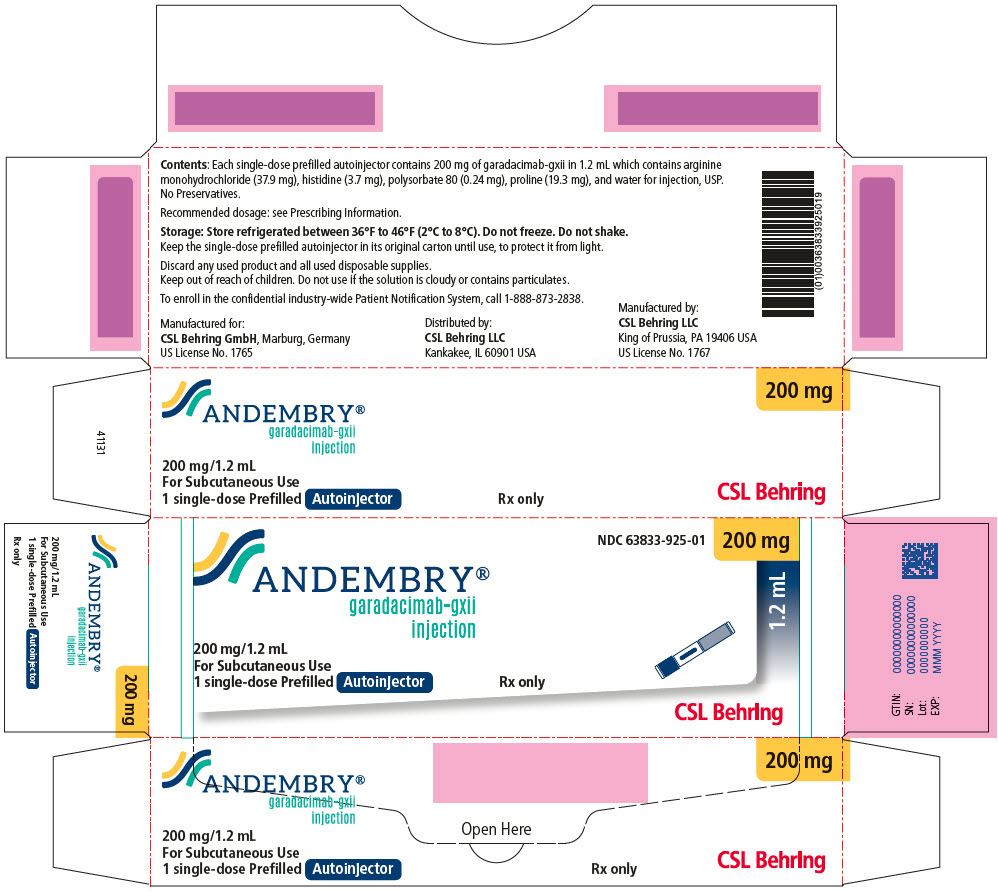 DRUG LABEL: ANDEMBRY
NDC: 63833-925 | Form: INJECTION, SOLUTION
Manufacturer: CSL
Category: prescription | Type: HUMAN PRESCRIPTION DRUG LABEL
Date: 20250630

ACTIVE INGREDIENTS: Garadacimab 200 mg/1.2 mL

HIGHLIGHTS OF PRESCRIBING INFORMATION

These highlights do not include all the information needed to use ANDEMBRY safely and effectively. See full prescribing information for ANDEMBRY.
ANDEMBRY® (garadacimab-gxii) injection, for subcutaneous use
Initial U.S. Approval: 2025

1 INDICATIONS AND USAGE

ANDEMBRY is an activated Factor XII (FXIIa) inhibitor (monoclonal antibody) indicated for prophylaxis to prevent attacks of hereditary angioedema (HAE) in adult and pediatric patients aged 12 years and older. (1)

2 DOSAGE AND ADMINISTRATION

- Recommended Dosage: Initial loading dose of 400 mg (two 200 mg injections) administered subcutaneously followed by maintenance dosage of 200 mg once monthly. (2.1)
- Subcutaneous use only. (2.2)
- Patients may self-administer. See full prescribing information for preparation and administration instructions. (2.2)

3 DOSAGE FORMS AND STRENGTHS

Injection:

- 200 mg/1.2 mL solution in single-dose prefilled autoinjector (3)
- 200 mg/1.2 mL (167 mg/mL) solution in single-dose prefilled syringe with needle safety device (3)

4 CONTRAINDICATIONS

None. (4)

5 WARNINGS AND PRECAUTIONS

None. (5)

6 ADVERSE REACTIONS

Most common adverse reactions (incidence ≥ 7%) are nasopharyngitis and abdominal pain. (6.1)

To report SUSPECTED ADVERSE REACTIONS, contact CSL Behring at 1-866-915-6958 or FDA at 1-800-FDA-1088 or www.fda.gov/medwatch.

7 DRUG INTERACTIONS

- Drug Interference with Laboratory Test: ANDEMBRY can prolong activated partial thromboplastin time (aPTT) due to an interaction of garadacimab-gxii with the aPTT assay. (7.1)

FULL PRESCRIBING INFORMATION

1 INDICATIONS AND USAGE

ANDEMBRY is indicated for prophylaxis to prevent attacks of hereditary angioedema (HAE) in adult and pediatric patients aged 12 years and older.

2 DOSAGE AND ADMINISTRATION

2.1 Recommended Dosage

The recommended dosage of ANDEMBRY is an initial loading dose of 400 mg (two injections of 200 mg) administered subcutaneously on the first day of treatment followed by a maintenance dosage of 200 mg administered subcutaneously every month.

Missed Dose(s)

If a dose of ANDEMBRY is missed, administer the dose as soon as possible.

2.2 Preparation and Administration Instructions for ANDEMBRY Prefilled Autoinjector and Prefilled Syringe with Needle Safety Device

- For subcutaneous use only.
- ANDEMBRY is intended for self-administration or administration by a caregiver. Prior to treatment initiation, train patients/caregivers on proper preparation and subcutaneous (SC) administration technique of ANDEMBRY [see Instructions for Use].
- Prior to administration, remove ANDEMBRY from the refrigerator and allow to sit for 30 minutes at room temperature before use.
- Inspect ANDEMBRY visually for particulate matter and discoloration prior to administration, whenever solution and container permit. ANDEMBRY is a slightly opalescent to clear, brownish-yellow to yellow solution.
- Administer ANDEMBRY subcutaneously into the thigh or abdomen ensuring to stay 1 inch (2 cm) away from the navel. The upper arm can also be used if a caregiver administers the subcutaneous injection.
- Discard the used ANDEMBRY into a sharps disposal container (closed puncture-resistant container).
- For detailed instructions on the preparation and administration of ANDEMBRY [see Instructions for Use].

3 DOSAGE FORMS AND STRENGTHS

Injection: a sterile, preservative-free, slightly opalescent to clear, brownish-yellow to yellow solution available in the following:

- 200 mg/1.2 mL of garadacimab solution in a single-dose prefilled autoinjector
- 200 mg/1.2 mL (167 mg/mL) of garadacimab solution in a single-dose prefilled syringe with needle safety device

4 CONTRAINDICATIONS

None.

5 WARNINGS AND PRECAUTIONS

None.

6 ADVERSE REACTIONS

6.1 Clinical Trials Experience

Because clinical trials are conducted under widely varying conditions, adverse reaction rates observed in the clinical trials of a drug cannot be directly compared to rates in the clinical trials of another drug and may not reflect the rates observed in practice.

The safety of ANDEMBRY reflects the exposure in a total of 164 adult and pediatric patients aged 12 years and older with hereditary angioedema (HAE) from a placebo-controlled study, VANGUARD [see Clinical Studies (14)], and an open-label clinical study. Among the 164 patients who received at least one dose of ANDEMBRY 200 mg subcutaneously, 153 (93%) patients were exposed for at least one year. The median duration of ANDEMBRY treatment was 2.6 years.

The safety data below is based on the 6-month placebo-controlled study (VANGUARD), in which ANDEMBRY 400 mg was administered subcutaneously as a loading dose followed by 200 mg (N=39) every month in patients with HAE. Demographics of the patients in this study are summarized in Clinical Studies [see Clinical Studies (14)]. The safety of ANDEMBRY was similar across all subgroups of patients, including analysis by age, sex and geographic region.

Table 1 provides the most common adverse reactions with ANDEMBRY with incidence ≥7% and more common than placebo.

Table 1 Adverse Reactions with ANDEMBRY with Incidence ≥7% and More Common than Placebo in Patients with HAE (VANGUARD)
Adverse Reactions | ANDEMBRY (N=39) | Placebo (N=25)
 | n (%) | n (%)
Nasopharyngitis [Consists of nasopharyngitis, rhinitis, and upper respiratory infections] | 8 (21) | 3 (12)
Abdominal Pain [Consists of abdominal pain and abdominal pain lower] | 3 (8) | 0

Specific Adverse Reaction(s):

Injection Site Reactions

In VANGUARD and an open-label clinical study, which included 57 patients who rolled over from VANGUARD, 164 patients with HAE received ANDEMBRY 200 mg subcutaneously every month. Injection site reactions (e.g., injection site bruising, injection site erythema, injection site hematoma, injection site pruritus, injection site urticaria) were reported in 23 (14%) patients.

Laboratory Abnormalities:

Prolonged Coagulation Tests (aPTT and PT)

In the VANGUARD trial, the incidence of prolonged activated partial thromboplastin time (aPTT), defined as >1.4×ULN, was 3 (8%) patients in the ANDEMBRY group compared to 0 patients in the placebo group. Additionally, the incidence of prolonged prothrombin time (PT) or international normalized ratio (INR), defined as >1.3× ULN, was 6 (15%) patients in the ANDEMBRY group compared to 1 (4%) patient in the placebo group. None of the increases in aPTT, PT and INR were associated with bleeding events [see Drug Interactions (7.1)].

7 DRUG INTERACTIONS

7.1 Drug Interference with Laboratory Test

Coagulation Tests

ANDEMBRY can prolong activated partial thromboplastin time (aPTT) due to an interaction of garadacimab-gxii with the aPTT assay. The reagents used in the aPTT laboratory test initiate intrinsic coagulation through the activation of FXII in the contact system, therefore inhibition of plasma FXIIa by ANDEMBRY can prolong aPTT in this assay [see Adverse Reactions (6.1)].

8 USE IN SPECIFIC POPULATIONS

8.1 Pregnancy

Risk Summary

There are no available data on ANDEMBRY use in pregnant women to evaluate for a drug-associated risk of major birth defects, miscarriage or other adverse maternal or fetal outcomes. Monoclonal antibodies such as garadacimab-gxii are transported across the placenta during the third trimester of pregnancy; therefore, potential effects on a fetus are likely to be greater during the third trimester of pregnancy. In an embryo-fetal development study in pregnant rabbits, garadacimab-gxii produced no evidence of fetal harm at doses up to approximately 100 times the exposure achieved at the maximum recommended human dose (MRHD) of 200 mg once monthly. In a pre- and post-natal development study in rabbits, garadacimab-gxii had no effects on survival, growth, or development of F1 offspring at doses resulting in approximately 76 times the exposure achieved at the MRHD (see Data).

The estimated background risk of major birth defects and miscarriage for the indicated population(s) is unknown. All pregnancies have a background risk of birth defect, loss, or other adverse outcomes. In the U.S. general population, the estimated background risk of major birth defects and miscarriage in clinically recognized pregnancies is 2% to 4% and 15% to 20%, respectively.

Data

Animal Data

In an embryo-fetal development study in pregnant rabbits dosed by the intravenous route every 3 days during the period of organogenesis from gestation days 6 to 18, garadacimab-gxii produced no evidence of fetal harm or maternal toxicity at doses resulting in approximately 100 times the exposure achieved at the MRHD (on an AUC basis with maternal intravenous doses up to 100 mg/kg/dose).

In a pre- and post-natal development study in rabbits dosed by the intravenous or subcutaneous route once every 5 days from the end of implantation (Gestation Day 7) to postpartum day 38 (end of the lactation period), garadacimab-gxii had no effects on survival, growth, or development of F1 offspring at doses resulting in approximately 76 times the exposure achieved at the MRHD (on an AUC basis with a maternal intravenous dose of 100 mg/kg/dose). There was no evidence of maternal toxicity.

Garadacimab-gxii crossed the placenta in rabbits. With a maternal dose of 100 mg/kg garadacimab-gxii on gestation day 29, fetal plasma concentrations were 40.8% of maternal concentrations following subcutaneous administration and approximately equivalent following intravenous administration.

8.2 Lactation

Risk Summary

There are no data on the presence of garadacimab-gxii or its metabolite in either human or animal milk, the effects on the breastfed infant, or the effects on milk production. Maternal IgG is known to be present in human milk. The effects of local gastrointestinal exposure and limited systemic exposure in the breastfed infant to garadacimab-gxii are unknown.

The developmental and health benefits of breastfeeding should be considered along with the mother's clinical need for ANDEMBRY and any potential adverse effects on the breastfed infant from ANDEMBRY or the underlying maternal condition.

8.4 Pediatric Use

The safety and effectiveness of ANDEMBRY for prophylaxis to prevent attacks of HAE have been established in pediatric patients aged 12 years and older. Use of ANDEMBRY for this indication is supported by evidence from a total of 6 pediatric patients aged 12 years and older enrolled in VANGUARD who received treatment with ANDEMBRY 400 mg loading dose administered subcutaneously followed by a maintenance dosage of 200 mg subcutaneously every month (n=4) or placebo (n=2). Results of the subgroup analysis for pediatric patients aged 12 years and older were consistent with study results for adult patients [see Adverse Reactions (6.1), Clinical Pharmacology (12.3), and Clinical Studies (14)].

The safety and effectiveness of ANDEMBRY have not been established in pediatric patients younger than 12 years of age.

8.5 Geriatric Use

Of the total number of ANDEMBRY-treated patients in the clinical study for prophylaxis to prevent attacks of HAE, 6 (9%) were 65 years of age and older [see Clinical Studies (14)]. No overall differences in safety or effectiveness of ANDEMBRY have been observed between patients 65 years of age and older and younger adult patients [see Adverse Reactions (6.1), Clinical Pharmacology (12.3), and Clinical Studies (14)].

11 DESCRIPTION

Garadacimab-gxii, an activated Factor XII (FXIIa) inhibitor, is a recombinant, fully human, monoclonal antibody (IgG4/λ-light chain) produced in Chinese Hamster Ovary (CHO) cells. Based on the amino acid sequence, the molecular weight of garadacimab-gxii is approximately 148 kDa.

ANDEMBRY (garadacimab-gxii) injection is a sterile, preservative-free, slightly opalescent to clear, brownish-yellow to yellow solution for subcutaneous use.

Each 1.2 mL prefilled autoinjector or prefilled syringe with needle safety device of ANDEMBRY contains 200 mg of garadacimab-gxii, arginine monohydrochloride (37.9 mg), histidine (3.7 mg), polysorbate 80 (0.24 mg), proline (19.3 mg), and water for injection, USP. The pH is 6.1.

12 CLINICAL PHARMACOLOGY

12.1 Mechanism of Action

Garadacimab-gxii is an inhibitor of activated FXII that binds to the catalytic domain of activated Factor XII (FXIIa and βFXIIa) and inhibits its catalytic activity. FXII is the first factor activated in the contact activation pathway and initiates the inflammatory bradykinin-producing kallikrein-kinin system. The inhibition of FXIIa decreases the activation of prekallikrein to kallikrein and the generation of bradykinin, which is associated with inflammation and swelling in HAE attacks, thus reducing the cascade of events leading to an HAE attack.

12.2 Pharmacodynamics

Garadacimab-gxii concentration-dependent inhibition of FXIIa-mediated kallikrein activity was observed in patients with HAE. Inhibition of FXIIa-mediated kallikrein activity was observed after the first dose.

12.3 Pharmacokinetics

The pharmacokinetics of garadacimab-gxii are provided in Table 2 following subcutaneous administration of a single 200 mg dose to healthy volunteers and are presented as mean (SD), unless otherwise specified.

Table 2 Garadacimab-gxii Pharmacokinetics Following Subcutaneous Administration [The PK of garadacimab-gxii is similar between healthy volunteers and subjects with HAE]
Parameter | Garadacimab-gxii
Exposure
Cmax | 18.4 (7.23) mcg/mL
AUC0-inf | 11470 (4103) mcg∙h/mL
Ctrough,Steady State [HAE patients enrolled in the VANGUARD trial] , [Garadacimab-gxii exposure (based on AUCtau and Cmax) following the initial subcutaneous administration of loading dose of 400 mg (2 doses of 200 mg) is 133% of steady-state exposures following 200 mg subcutaneous once monthly.] | 8.09 (4.28) to 8.69 (3.93) mcg /mL
Absorption
Absolute Bioavailability | 39 (34, 43)%
Tmax | 6 (2, 15) days
Distribution
Apparent Volume of Distribution | 11.8 (5.17) Liters (L)
Elimination
Half-Life | 17.4 (3.14) days
Apparent Clearance | 0.02 (0.008) L/h
Metabolism
Primary Pathway | Expected to be metabolized into small peptides by catabolic pathways
Abbreviations: AUC = area under the plasma concentration-time curve; CI = confidence interval; Cmax = maximum plasma concentration; Ctrough,steady state = trough plasma concentration at steady state; Tmax = time to peak concentration
Tmax is reported as median (range) and absolute bioavailability is reported as estimate (95% CI)

Specific Populations

No clinically significant differences in the pharmacokinetics of garadacimab-gxii were observed based on age (age range: 12 to 73 years), gender, race, body weight (range: 43 to 153 kg), and mild to moderate renal impairment (eGFR 30 to <90 mL/min/1.73 m^2). The effect of severe renal impairment (eGFR <30 mL/min/1.73 m^2) on garadacimab-gxii pharmacokinetics is unknown.

Pediatric Patients

No clinically significant difference in garadacimab-gxii Cmax and AUCtau was observed between pediatric patients (age range: 12 to 17 years) and adults who received the recommended dosage of garadacimab-gxii (200 mg of garadacimab-gxii once monthly).

Drug Interactions

No dedicated drug interaction studies have been conducted in humans.

12.6 Immunogenicity

The observed incidence of anti-drug antibodies (ADA) is highly dependent on the sensitivity and specificity of the assay. Differences in assay methods preclude meaningful comparisons of the incidence of anti-drug antibodies in the studies described below with the incidence of anti-drug antibodies in other studies, including those of garadacimab-gxii or other garadacimab products.

In VANGUARD, 2.6% (1/39) of patients who received garadacimab-gxii tested positive for anti- garadacimab-antibodies during the 6-month treatment period.

The development of ADA against garadacimab-gxii did not affect pharmacokinetics (PK), safety, or clinical response.

13 NONCLINICAL TOXICOLOGY

13.1 Carcinogenesis, Mutagenesis, Impairment of Fertility

Animal studies have not been conducted to evaluate the carcinogenic or mutagenic potential of garadacimab-gxii.

Fertility and reproductive performance were unaffected in sexually mature male and female rabbits that received garadacimab-gxii at intravenous doses up to 100 mg/kg once every three days (resulting in exposures in male and female rabbits up to approximately 100 and 80 times the MRHD on an AUC basis).

14 CLINICAL STUDIES

The efficacy of ANDEMBRY for prophylaxis to prevent hereditary angioedema (HAE) attacks was evaluated in a multicenter, randomized, double-blind, placebo-controlled, parallel-group study (VANGUARD [NCT04656418]) of 6 months duration.

VANGUARD enrolled a total of 64 adult and pediatric patients 12 years of age and older with Type I or Type II HAE who experienced at least 2 investigator-confirmed HAE attacks over a 2-month period prior to treatment with ANDEMBRY or placebo. Patients were randomized in a 3:2 ratio (ANDEMBRY:placebo) to receive an initial loading dose of ANDEMBRY 400 mg administered subcutaneously followed by a maintenance dose of 200 mg every month, or matched placebo. Patients were required to discontinue other prophylactic HAE medications prior to entering the study. All patients were allowed to use on-demand medications for the treatment of HAE attacks during the study.

The demographics and baseline characteristics of patients in VANGUARD are provided in Table 3.

Table 3 Demographics and Baseline Characteristics of Patients in the VANGUARD Trial
 | VANGUARD (N=64)
Female, n (%) | 38 (59)
Race, n (%)
Asian | 6 (9)
Black or African American | 1 (2)
Native Hawaiian or Pacific Islander | 1 (2)
White | 55 (86)
Other | 1 (2)
Hispanic or Latino, n (%) | 3 (5)
Mean age, years (SD) | 41 (16)
≤ 17 years, n (%) | 6 (9)
> 17 years, n (%) | 58 (91)
C1-INH HAE Type 1, n (%) | 56 (88)
Prior HAE prophylaxis [Within 3 months before screening] , n (%) | 21 (33)
Baseline HAE attack rate [During 2-month period prior to treatment] , n (%)
1 to < 3 attacks | 26 (41)
≥ 3 attacks | 38 (59)

The primary endpoint for VANGUARD was the monthly HAE attack rate at 6 months (number of investigator-confirmed HAE attacks per month). As shown in Table 4, the least squares mean for the monthly HAE attack rate was lower with ANDEMBRY compared to placebo.

Table 4 Rate of Monthly HAE Attack at 6 Months in VANGUARD
Rate of Monthly HAE Attack | ANDEMBRY (N=39) | Placebo (N=25)
LS mean (95% CI) | 0.22 (0.11, 0.47) | 2.07 (1.49, 2.87)
Percent reduction relative to placebo (95% CI) | 89.2 (75.6, 95.2)
P-value [Obtained from a two-sided Wilcoxon rank sum test at alpha = 5%] | < 0.001
Abbreviations: CI=confidence interval; HAE=hereditary angioedema; LS=least squares
Note: LS means were obtained from a Poisson model accounting for overdispersion with an offset term for time on treatment and fixed effects for treatment group and HAE attack rate over a 2-month period prior to treatment

The monthly rate of HAE attacks requiring on-demand therapy and the monthly rate of moderate or severe HAE attacks were assessed as secondary endpoints in VANGUARD. There was a 91.2% reduction with ANDEMBRY relative to placebo in the monthly rate of HAE attacks requiring on-demand therapy and a 93.6% reduction with ANDEMBRY relative to placebo in the monthly rate of moderate or severe HAE attacks.

Additional secondary endpoints assessed the proportion of patients with a ≥50%, ≥70%, ≥90%, and 100% (attack-free) reduction in monthly HAE attack rate from the first dose through the end of the 6-month treatment period compared to the 2-month period prior to treatment. The proportion of patients with a ≥50%, ≥70%, ≥90%, and 100% reduction was 95%, 92%, 74%, and 62% on ANDEMBRY versus 33%, 17%, 8%, and 0% on placebo, respectively.

16 HOW SUPPLIED/STORAGE AND HANDLING

How Supplied

ANDEMBRY (garadacimab-gxii) injection is a ready-to-use, slightly opalescent to clear, brownish-yellow to yellow solution in the following presentations, supplied in single-dose prefilled autoinjector or prefilled syringe with needle safety device.

Table 5 provides the available presentations and strengths of ANDEMBRY.

Table 5 Presentations and Strengths for ANDEMBRY
Presentation | Strength | Unit Count | NDC (Device) | NDC (Carton)
Prefilled autoinjector | 200 mg/1.2 mL | 1 | 63833-925-20 | 63833-925-01
Prefilled syringe with needle safety device | 200 mg/1.2 mL (167 mg/mL) | 1 | 63833-920-20 | 63833-920-01

Each single-dose prefilled autoinjector or prefilled syringe with needle safety device is supplied in a carton.

Storage and Handling

- Do not freeze. Do not shake.
- Keep the prefilled autoinjector and prefilled syringe with needle safety device in the original carton to protect from light.
- Store the prefilled autoinjector and prefilled syringe with needle safety device refrigerated at 36°F to 46°F (2°C - 8°C).

17 PATIENT COUNSELING INFORMATION

Advise the patient to read the FDA-approved patient labeling (Patient Information and Instructions for Use).

Administration Instructions

- Instruct patients that ANDEMBRY is for subcutaneous use and intended for self-administration or administration by caregiver.
- Instruct patients and/or caregivers on the proper preparation and subcutaneous administration techniques of ANDEMBRY [see Dosage and Administration (2.2) and Instructions for Use].
- Instruct patients and/or caregivers to administer ANDEMBRY subcutaneously into the upper arm, thigh or abdomen ensuring to stay 1 inch (2 cm) away from the navel [see Dosage and Administration (2.2)].
- Instruct patients or caregivers in proper disposal technique for prefilled autoinjector or prefilled syringe with needle safety device and advise them not to reuse these items.
- Instruct patients to dispose of the prefilled autoinjector or prefilled syringe with needle safety device in a sharps disposal container (closed puncture-resistant container).

Manufactured for:
CSL Behring GmbH
Emil-von-Behring-Strasse 76,
35041 Marburg, Germany
US License No. 1765

Manufactured by:
CSL Behring LLC
King of Prussia, PA 19406
US License No. 1767

Distributed by:
CSL Behring LLC
Kankakee, IL 60901

For more information, visit www.ANDEMBRY.com

For Patent information: www.cslbehring.com/products/patents

PATIENT INFORMATION
ANDEMBRY ® (an-DEM-bree)
(garadacimab-gxii)
injection, for subcutaneous use

Read this Patient Information before you start using ANDEMBRY and each time you get a refill. There may be new information. This information does not take the place of talking with your healthcare provider about your medical condition or treatment.

What is ANDEMBRY?
ANDEMBRY is a prescription medicine used to prevent attacks of Hereditary Angioedema (HAE) in children 12 years of age and older.
It is not known if ANDEMBRY is safe and effective in children under 12 years of age.

Before you use ANDEMBRY, tell your healthcare provider about all of your medical conditions, including if you:

- are pregnant or planning to become pregnant. It is not known if ANDEMBRY can harm your unborn baby.
- are breastfeeding or plan to breastfeed. It is not known if ANDEMBRY passes into your breastmilk. Talk to your healthcare provider about the best way to feed your baby while using ANDEMBRY.

Tell your healthcare provider about all the medicines you take, including prescription medicines, over-the-counter medicines, vitamins and herbal supplements.

How should I use ANDEMBRY?

- See the detailed Instructions for Use that comes with this Patient Information leaflet about the right way to prepare and inject ANDEMBRY.
- Use ANDEMBRY exactly as your healthcare provider tells you to use it.
- ANDEMBRY is given as an injection under your skin (subcutaneous) by you or a caregiver.
- Your healthcare provider should show you or your caregiver how to prepare and inject your dose of ANDEMBRY before you inject yourself for the first time.
- Do not try to inject ANDEMBRY unless you have been trained by your healthcare provider.

What are the possible side effects of ANDEMBRY?
The most common side effects of ANDEMBRY include:

- redness, itchiness, and bruising (injection site reactions)
- stomach (abdominal) pain
- runny or stuffy nose, sneezing, watery eyes (nasopharyngitis)

Tell your healthcare provider if you have any side effect that bothers you or that does not go away. These are not all the possible side effects of ANDEMBRY. For more information, ask your healthcare provider or pharmacist.
Call your doctor for medical advice about side effects. You may report side effects to FDA at 1-800-FDA-1088.

General information about the safe and effective use of ANDEMBRY
Medicines are sometimes prescribed for purposes other than those listed in a Patient Information leaflet. Do not use ANDEMBRY for a condition for which it is not prescribed. Do not give ANDEMBRY to other people, even if they have the same symptoms that you have. It may harm them. You can ask your pharmacist or healthcare provider for information about ANDEMBRY that is written for healthcare professionals.

What are the ingredients in ANDEMBRY?
Active ingredient: garadacimab-gxii
Inactive ingredients: arginine monohydrochloride, histidine, polysorbate 80, proline, water for injection.
Manufactured for:
CSL Behring GmbH
Emil-von-Behring-Strasse 76,
35041 Marburg, Germany
US License No. 1765
Manufactured by:
CSL Behring LLC
King of Prussia, PA 19406
US License No. 1767
Distributed by:
CSL Behring LLC
Kankakee, IL 60901
For Patent information: www.cslbehring.com/products/patents
For more information, visit www.ANDEMBRY.com or call 1-866-915-6158.

This Patient Information has been approved by the U.S. Food and Drug Administration.
Revised 06/2025

INSTRUCTIONS FOR USE
ANDEMBRY (an-DEM-bree)
(garadacimab-gxii)
injection, for subcutaneous use
Prefilled Autoinjector

Important:
This autoinjector works differently than other injection devices. Read the Instructions for Use carefully before using it, and each time you get a new autoinjector. There may be new information. This information does not take the place of talking to your healthcare provider about your medical condition or treatment.
Children should inject ANDEMBRY under the supervision of an adult.
Make sure you have been trained by your healthcare provider before you use this autoinjector for the first time.

Parts of the Autoinjector (see Figure A):

Continue to the next sections to prepare and perform the injection.

Figure A

Read the Following Safety Information:

- Keep the autoinjector in its original carton box until use, to protect it from light.
- Do not remove the clear autoinjector cap until you are ready to inject.
- Do not put the clear autoinjector cap back on the autoinjector after it has been removed because this could start the injection and cause injury.
- The autoinjector contains 1 dose and is for one time use only. Do not try to reuse the same autoinjector.
- Do not use the autoinjector if the expiration date has passed.
- The autoinjector is for subcutaneous (under the skin) injection only.
- Do not use the autoinjector if it has dropped, looks damaged, has cracks, or is leaking medicine. Throw away the autoinjector as described in Step 11 and use a new one.
- Do not inject through clothing.
- Do not touch or try to remove the gray needle shield at any time.
- Keep ANDEMBRY and all medicines out of reach of children.

Contact your healthcare provider if you have any questions.

How Should I Store ANDEMBRY?

- Store ANDEMBRY autoinjector in a refrigerator, between 36°F to 46°F (2°C to 8°C) in its original carton box until use, to protect it from light.
- Do not shake
- Do not freeze. If the autoinjector has been frozen, do not use the autoinjector even if it is thawed.
- The refrigerated autoinjector may be used until the expiration date (EXP) printed on the label.
- Take the autoinjector out of the refrigerator 30 minutes before use, allowing it to reach room temperature.
- Do not put the autoinjector back in the refrigerator after it has reached room temperature.

Supplies needed for your Autoinjector Injection (see Figure B):

Included in the carton box:

- 1 Single-dose autoinjector

Required supplies but not included in the carton box:

- 1 Alcohol pad
- 1 Cotton ball or gauze pad
- 1 FDA-cleared sharps container or puncture-resistant container for disposal (see Step 11. Disposing of the Autoinjector)

Figure B

Preparing for an Injection

Do not remove the clear autoinjector cap until immediately before the injection.

Step 1. Let the Autoinjector Reach Room Temperature

- Remove the autoinjector from the carton box and place it laying down on a clean flat surface.
- Wait 30 minutes for the medicine to reach room temperature after taking it out of the refrigerator (see Figure C).
- Injecting the medicine cold could be uncomfortable.
- Do not try to speed up the warming process in any way. For example, do not warm it in a microwave, in hot water, or leave it in direct sunlight.

Figure C

Step 2. Check the Expiration Date

- Check the expiration date on the autoinjector label (see Figure D).
- Do not use the autoinjector if the expiration date has passed.
- If the expiration date has passed, then safely dispose of the autoinjector and get a new one (see Step 11. Disposing of the Autoinjector).

Figure D

Step 3. Inspect the autoinjector and the medicine

- Check the autoinjector for damage.
- Check the medicine through the viewing window of the autoinjector (see Figure E).
- It is normal to see air bubbles, do not try to remove the air bubbles.
- The medicine should be brownish-yellow to yellow and may appear slightly opalescent to clear.
- Do not use the autoinjector, safely dispose and get a new one (see Step 11. Disposing of the Autoinjector) if:
  - The medicine is discolored or contains particles
  - The autoinjector looks damaged or has cracks
  - The autoinjector is leaking
  - The autoinjector has been dropped on a hard surface, even if it does not look damaged

Figure E

Choose and Prepare an Injection Site

Step 4. Clean your Hands

- Wash your hands well with soap and water or use hand sanitizer (see Figure F).

Figure F

Step 5. Select the Injection Site

- Inject into the thigh or belly (abdomen) area, but stay 1 inch (2 cm) away from the belly button (navel) (see Figure G)
- If somebody else (caregiver) gives you the injection, they can also use the upper arm. Do not try to inject into the upper arm yourself.
- Change (rotate) your injection site with each injection. Do not inject in the same place multiple times if the skin is damaged.
- Do not inject into the belly button, moles, scars or bruises, or into areas where the skin is tender, red, hard, or injured.

Figure G

Step 6. Prepare the Injection Site

- Clean the injection site with an alcohol pad (see Figure H).
- Let your skin dry on its own.
- Do not touch this area again before injecting.
- Do not fan or blow on the skin area that you cleaned.

Figure H

Injecting the Medicine with the Autoinjector

Complete the Injection without stopping. Read all steps first before beginning.

Do not remove the Clear Cap until you are ready to inject.

Step 7. Remove Clear Autoinjector Cap and Dispose of the Cap

- Hold the autoinjector with one hand and pull the Clear Autoinjector Cap straight off with the other hand.
- Do not twist the Clear Cap, (see Figure I). If you cannot remove the Clear Cap, ask a caregiver for help or contact your healthcare provider.
- The Clear Cap has a metal part inside, this is normal.
- Do not put the Clear Cap back on after it has been removed, because this could start the injection and cause injury.
- Dispose of the Clear Cap in an FDA-cleared sharps container.

Important:

- Do not touch the gray needle shield of the autoinjector to avoid injury.
- Do not put the autoinjector down after removing the Clear Cap.

Figure I

Step 8. Pinch the Skin and place the autoinjector on the injection site

Immediately after removing the clear autoinjector cap, complete the following steps without stopping:

- Gently pinch the area of cleaned skin around the injection site and hold the area firmly until the injection is complete (see Figure J).
- Place the autoinjector at a 90° angle on the cleaned injection site (see Figure J).
- Make sure you can see the viewing window.

Figure J

Step 9. Inject Medicine (see Figure K)

You Must Read all of Step 9 before injecting.
The injection may take up to 15 seconds.
To ensure you receive a full dose you must keep the autoinjector firmly pressed against your pinched skin until:

- The yellow plunger has stopped moving and filled the viewing window, and
- 5 seconds has passed after the 2nd "Click."

Press the gray needle shield down firmly against the pinched skin to start the injection and keep pressing down until all the steps below are complete.
Press down to start | Keep Pressing Down | Keep Pressing down for 5 more seconds …1…2…3…4…5
Press down to start the injection and listen for a First 'Click'.; - The First "Click" means the injection has started. - The yellow plunger will start moving in the viewing window. | Keep pressing the autoinjector down and watch the viewing window.; - The window will turn yellow and - You will hear a Second 'Click'. | Keep pressing the autoinjector down for 5 more seconds to make sure you get the full dose. Make sure the yellow plunger completely fills the window and has stopped moving before you remove the autoinjector.
Keep pressing the autoinjector down. | Keep pressing the autoinjector down.
Figure K

- Do not remove the autoinjector until the yellow plunger has stopped moving and completely filled the viewing window, and 5 seconds has passed after the Second "Click."
- Do not remove, tilt, or rotate the autoinjector during the injection.

Step 10. Release the Pinch and Remove the Autoinjector

- Release the pinch and remove the autoinjector at a 90° angle from the skin (see Figure L).
- As the autoinjector is lifted from the skin, the gray needle shield returns to the original (before use) position, and will lock into place, covering the needle.

Figure L

Important: If you think that you have not received the full dose, contact your healthcare provider right away.

- If there is a little bleeding at the injection site, you can press a cotton ball or gauze over the injection site.
- Do not rub the injection site.
- If needed, you may cover the injection site with a small adhesive bandage.

Disposal

Step 11. Disposing of the autoinjector

- Do not try to reuse the autoinjector.
- After injecting your dose, put the autoinjector into an FDA-cleared sharps container or closed puncture-resistant container (see Figure M).

Figure M

- If you do not have an FDA-cleared sharps container, you may use a household container that is:
  - Made of heavy-duty plastic
  - Can be closed with a tight-fitting, puncture-resistant lid, without sharps being able to come out
  - Upright stable during use
  - Leak-resistant
  - Properly labeled to warn of hazardous waste inside the container
- When your sharps container is almost full, you will need to follow your local guidelines for the right way to dispose of your sharps container. There may be state or local laws about how you should throw away used needles and syringes. For more information, go to the FDA's website at: http://www.fda.gov/safesharpsdisposal.
- Do not dispose of your used sharps container in your household trash unless your local guidelines permit this.
- Do not recycle your used sharps container.

Step 12. Keep Track of Your Treatment

- If required by your healthcare provider, record your injection in a diary to help keep track of your medicine.

Manufactured by:
CSL Behring LLC
King of Prussia, PA 19406
US License No. 1767

This Instructions for Use has been approved by the U.S. Food and Drug Administration.
06/2025

PRINCIPAL DISPLAY PANEL - 200 mg Autoinjector Label

NDC 63833-925-20

200 mg
1.2 mL

ANDEMBRY®
garadacimab-gxii
injection

200 mg/1.2 mL
For Subcutaneous Use
1 single-dose Prefilled Autoinjector
Rx only

Manufactured by:
CSL Behring LLC
King of Prussia, PA
19406 USA
US License No. 1767

LOT 0000000000
EXP MMM YYYY

Read the instructions
before use

41126

PRINCIPAL DISPLAY PANEL - 200 mg Autoinjector Carton

NDC 63833-925-01

200 mg
1.2 mL

ANDEMBRY®
garadacimab-gxii
injection

200 mg/1.2 mL
For Subcutaneous Use
1 single-dose Prefilled Autoinjector
Rx only

CSL Behring